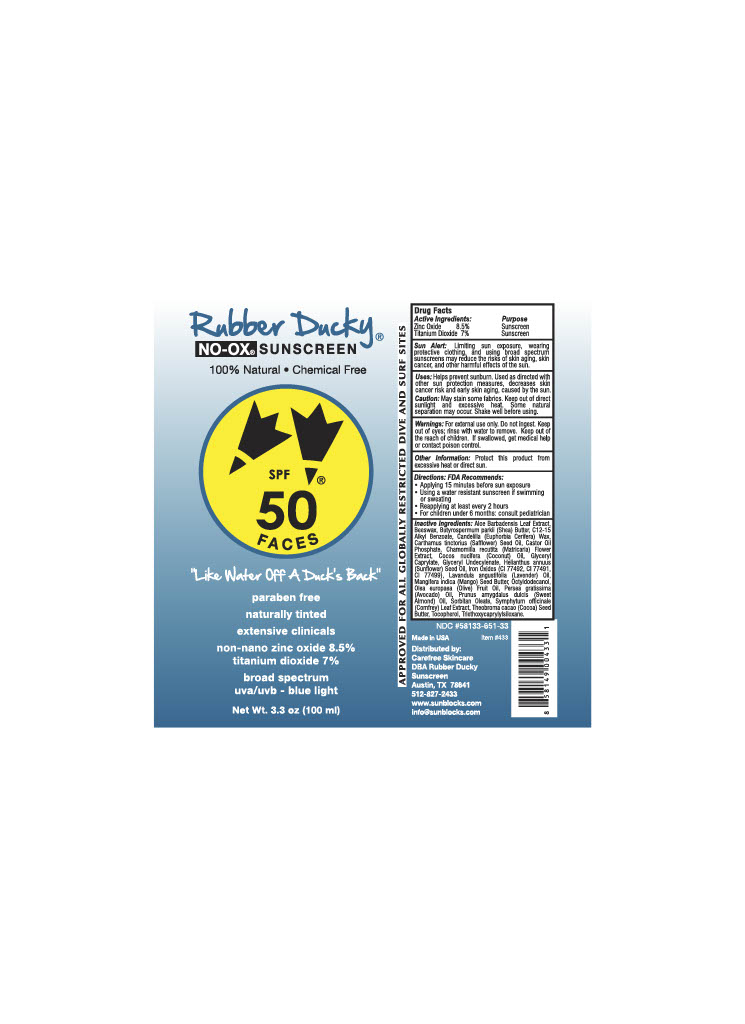 DRUG LABEL: SPF 50
NDC: 58133-651 | Form: LOTION
Manufacturer: Cosmetic Specialty Labs, Inc.
Category: otc | Type: HUMAN OTC DRUG LABEL
Date: 20211108

ACTIVE INGREDIENTS: ZINC OXIDE 8.5 g/100 mL; TITANIUM DIOXIDE 7 g/100 mL
INACTIVE INGREDIENTS: TOCOPHEROL; YELLOW WAX; COCONUT OIL; COCOA BUTTER; SAFFLOWER OIL; GLYCERYL 1-UNDECYLENATE; OLIVE OIL; TRIETHOXYCAPRYLYLSILANE; CHAMOMILE; MANGIFERA INDICA SEED BUTTER; SHEA BUTTER; AVOCADO OIL; GLYCERYL CAPRYLATE; SUNFLOWER OIL; ALMOND OIL; ALKYL (C12-15) BENZOATE; CANDELILLA WAX; LAVENDER OIL; ALOE VERA LEAF; COMFREY; CASTOR OIL; OCTYLDODECANOL; FERRIC OXIDE YELLOW; SORBITAN MONOOLEATE; FERRIC OXIDE RED; FERROSOFERRIC OXIDE

Active Ingredients

Zinc Oxide

Titanium Dioxide

Purpose

Sunscreen

Sunscreen

Sun Alert:

Limiting sun exposure, wearing protective clothing, and using broad spectrum sunscreens may reduce the risks of skin aging, skin cancer, and other harmful effects of the sun.

Uses

Helps prevent sunburn. Used as directed with other sun proctection measures, decreases skin cancer risk and early skin aging, caused by the sun.

Caution

May stain some fabrics. Keep out of direct sunlight and excessive heat. Some natural seperation may occur. Shake well before using.

Warnings

For external use only. Do not ingest. Keep out of eyes; rinse with water to remove. Keep out of reach of children. If swallowed, get medical help or contact poison control.

Other Information:

Protect this product from excessive heat or direct sun.

Directions: FDA Recommends

- Applying 15 minutes before sun exposure
- Using a water resistant sunscreen if swimming or sweating
- Reapplying at least every 2 hours
- For children under 6 months: consult pediatrician

Inactive Ingredients

Aloe Barbadensis Leaf Extract, Beeswax, Butyrospermum parkii (Shea) Butter, C12-15 Alkyl Benzoate, Candelilla (Euphorbia Cerifera) Wax, Carthamus tinctorius (Safflower) Seed Oil, Castor Oil Phosphate, Chamomilla recutita (Matricaria) Flower Extract, Cocos nucifera (Coconut) Oil, Glyceryl Caprylate, Glyceryl Undecylenate, Helianthus annuus (Sunflower) Seed Oil, Iron Oxides (CI 77492, CI 77491, CI 77499), Lavandula angustifolia (Lavender) Oil, Mangifera indica (Mango) Seed Butter, Octyldodecanol, Olea europaea (Olive) Fruit Oil, Persea gratissima (Avocado) Oil, Prunus amygdalus dulcis (Sweet Almond Oil), Sorbitan Oleate, Symphytum officinale (Comfrey) Leat Extract, Theobroma cacao (Cocoa) Seed Butter, Tocopherol, Triethoxycaprylylsiloxane